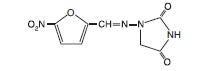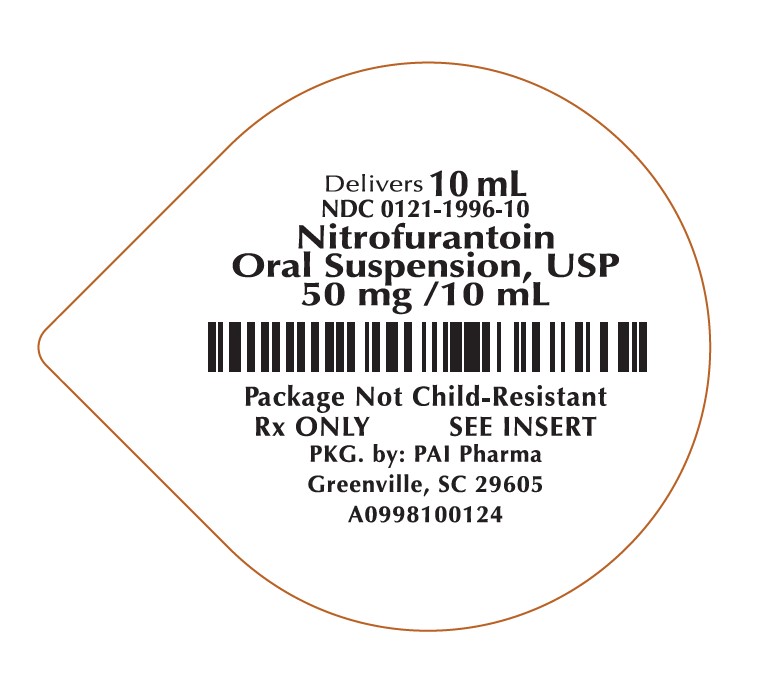 DRUG LABEL: Nitrofurantoin Oral Suspension
NDC: 0121-1996 | Form: SUSPENSION
Manufacturer: PAI Holdings, LLC dba PAI Pharma
Category: prescription | Type: HUMAN PRESCRIPTION DRUG LABEL
Date: 20251121

ACTIVE INGREDIENTS: NITROFURANTOIN 25 mg/5 mL
INACTIVE INGREDIENTS: CARBOXYMETHYLCELLULOSE SODIUM; ANHYDROUS CITRIC ACID; GLYCERIN; MAGNESIUM ALUMINUM SILICATE; METHYLPARABEN; PROPYLPARABEN; WATER; SODIUM CITRATE; SORBITOL; SUCRALOSE

NITROFURANTOIN ORAL SUSPENSION, USP
FOR ORAL USE ONLY
Rx Only

DESCRIPTION

Nitrofurantoin, a synthetic chemical, is a stable, yellow, crystalline compound. Nitrofurantoin Oral Suspension, USP is an antibacterial agent for specific urinary tract infections.

Nitrofurantoin Oral Suspension, USP is available in 25 mg/5 mL liquid suspension for oral administration.

Inactive Ingredients:

Nitrofurantoin Oral Suspension, USP contains carboxymethylcellulose sodium, citric acid, glycerin, magnesium aluminum silicate, methylparaben, N&A fruit gum flavor #960 (MN72), propylparaben, purified water, sodium citrate, sorbitol, and sucralose.

CLINICAL PHARMACOLOGY

Orally administered Nitrofurantoin Oral Suspension, USP is readily absorbed and rapidly excreted in urine. Blood concentrations at therapeutic dosage are usually low. It is highly soluble in urine, to which it may impart a brown color.

Following a dose regimen of 100 mg q.i.d. for 7 days, average urinary drug recoveries (0 to 24 hours) on day 1 and day 7 were 42.7% and 43.6%.

Unlike many drugs, the presence of food or agents delaying gastric emptying can increase the bioavailability of Nitrofurantoin Oral Suspension, USP, presumably by allowing better dissolution in gastric juices.

Microbiology:

Mode of Action
Nitrofurantoin is reduced by a wide range of enzymes including bacterial flavoproteins to reactive intermediates which are damaging to macromolecules such as DNA and proteins.

Cross-Resistance
Although cross-resistance with other antimicrobials may occur, cross resistance with sulfonamides has not been observed.

Interaction with Other Antimicrobials
Antagonism has been demonstrated in vitro between nitrofurantoin and quinolone antimicrobial agents. Nitrofurantoin, in the form of Nitrofurantoin Oral Suspension, USP,
has been shown to be active against most strains of the following bacteria both in vitro and in clinical infections: (See INDICATIONS AND USAGE).

Gram-Positive Aerobes

- Staphylococcus aureus
- Enterococcus species

Gram-Negative Aerobes

- Escherichia coli

NOTE: Some strains of Enterobacter species and Klebsiella species are resistant to nitrofurantoin.

The following in vitro data are available, but their clinical significance is unknown. Nitrofurantoin exhibits in vitro activity against the following bacteria; however, the safety and effectiveness of nitrofurantoin in treating clinical infections due to these bacteria have not been established in adequate and well controlled clinical trials.

Gram-Positive Aerobes

- Coagulase-negative staphylococci (including Staphylococcus epidermidis and Staphylococcus saprophyticus)
- Streptococcus agalactiae
- Viridans group streptococci

Gram-Negative Aerobes

- Citrobacter koseri
- Citrobacter freundii
- Klebsiella oxytoca

Nitrofurantoin is not active against most strains of Proteus species or Serratia species. It has no activity against Pseudomonas species.

Susceptibility Testing
For specific information regarding susceptibility test interpretive criteria, and associated test methods and quality control standards recognized by FDA for this drug, please see:
http://www.fda.gov/STIC.

INDICATIONS AND USAGE

Nitrofurantoin Oral Suspension, USP is specifically indicated for the treatment of urinary tract infections when due to susceptible strains of Escherichia coli, enterococci, Staphylococcus aureus, and certain susceptible strains of Klebsiella and Enterobacter species.

Nitrofurantoin is not indicated for the treatment of pyelonephritis or perinephric abscesses.

Nitrofurantoins lack the broader tissue distribution of other therapeutic agents approved for urinary tract infections. Consequently, many patients who are treated with Nitrofurantoin Oral Suspension, USP are predisposed to persistence or reappearance of bacteriuria. Urine specimens for culture and susceptibility testing should be obtained before and after completion of therapy. If persistence or reappearance of bacteriuria occurs after treatment with Nitrofurantoin Oral Suspension, USP, other therapeutic agents with broader tissue distribution should be selected. In considering the use of Nitrofurantoin Oral Suspension, USP, lower eradication rates should be balanced against the increased potential for
systemic toxicity and for the development of antimicrobial resistance when agents with broader tissue distribution are utilized.

CONTRAINDICATIONS:

Anuria, oliguria, or significant impairment of renal function (creatinine clearance under 60 mL per minute or clinically significant elevated serum creatinine) are contraindications. Treatment of this type of patient carries an increased risk of toxicity because of impaired excretion of the drug.

Because of the possibility of hemolytic anemia due to immature erythrocyte enzyme systems (glutathione instability), the drug is contraindicated in pregnant patients at term (38 to 42 weeks gestation), during labor and delivery, or when the onset of labor is imminent. For the same reason, the drug is contraindicated in neonates under one month of age.

Nitrofurantoin Oral Suspension, USP is contraindicated in patients with a previous history of cholestatic jaundice/hepatic dysfunction associated with nitrofurantoin. Nitrofurantoin
Oral Suspension, USP is also contraindicated in those patients with known hypersensitivity to nitrofurantoin.

WARNINGS:

Pulmonary reactions:
ACUTE, SUBACUTE, OR CHRONIC PULMONARY REACTIONS
HAVE BEEN OBSERVED IN PATIENTS TREATED WITH NITROFURANTOIN. IF THESE REACTIONS OCCUR, NITROFURANTOIN ORAL SUSPENSION, USP SHOULD BE DISCONTINUED AND APPROPRIATE MEASURES TAKEN. REPORTS HAVE CITED PULMONARY REACTIONS AS A CONTRIBUTING CAUSE OF DEATH.

CHRONIC PULMONARY REACTIONS (DIFFUSE INTERSTITIAL PNEUMONITIS OR PULMONARY FIBROSIS, OR BOTH) CAN DEVELOP INSIDIOUSLY. THESE REACTIONS OCCUR RARELY AND GENERALLY IN PATIENTS RECEIVING THERAPY FOR SIX MONTHS OR LONGER. CLOSE MONITORING OF THE PULMONARY CONDITION OF PATIENTS RECEIVING LONG-TERM THERAPY IS WARRANTED AND REQUIRES THAT THE BENEFITS OF THERAPY BE WEIGHED AGAINST POTENTIAL RISKS. (SEE RESPIRATORY REACTIONS.)

Hepatotoxicity:
Hepatic reactions, including hepatitis, cholestatic jaundice, chronic active hepatitis, and hepatic necrosis, occur rarely. Fatalities have been reported. The onset of chronic active hepatitis may be insidious, and patients should be monitored periodically for changes in biochemical tests that would indicate liver injury. If hepatitis occurs, the drug should be withdrawn immediately and appropriate measures should be taken.

Neuropathy:
Peripheral neuropathy, which may become severe or irreversible, has occurred. Fatalities have been reported. Conditions such as renal impairment (creatinine clearance under
60 mL per minute or clinically significant elevated serum creatinine), anemia, diabetes mellitus, electrolyte imbalance, vitamin B deficiency, and debilitating disease may enhance the occurrence of peripheral neuropathy. Patients receiving long-term therapy should be monitored periodically for changes in renal function.

Optic neuritis has been reported rarely in postmarketing experience with nitrofurantoin formulations.

Hemolytic anemia:
Cases of hemolytic anemia of the primaquine-sensitivity type have been induced by nitrofurantoin. Hemolysis appears to be linked to a glucose-6-phosphate dehydrogenase deficiency in the red blood cells of the affected patients. This deficiency is found in 10 percent of Blacks and a small percentage of ethnic groups of Mediterranean and Near- Eastern origin. Hemolysis is an indication for discontinuing Nitrofurantoin Oral Suspension, USP; hemolysis ceases when the drug is withdrawn.

Clostridium difficile-associated diarrhea:
Clostridium difficile associated diarrhea (CDAD) has been reported with use of nearly all antibacterial agents, including Nitrofurantoin Oral Suspension, USP, and may range in
severity from mild diarrhea to fatal colitis. Treatment with antibacterial agents alters the normal flora of the colon leading to overgrowth of C. difficile.

C. difficile produces toxins A and B which contribute to the development of CDAD. Hypertoxin producing strains of C. difficile cause increased morbidity and mortality, as these infections can be refractory to antimicrobial therapy and may require colectomy. CDAD must be considered in all patients who present with diarrhea following antibiotic use. Careful medical history is necessary since CDAD has been reported to occur over two months after the administration of antibacterial agents. If CDAD is suspected or confirmed, ongoing antibiotic use not directed against C. difficile may need to be discontinued. Appropriate fluid and electrolyte management, protein supplementation, antibiotic treatment of C. difficile, and surgical evaluation should be instituted as clinically indicated.

PRECAUTIONS

Information for Patients:

Patients should be advised to take Nitrofurantoin Oral Suspension, USP with food to further enhance tolerance and improve drug absorption. Patients should be instructed to complete the full course of therapy; however, they should be advised to contact their physician if any unusual symptoms should occur during therapy.

Diarrhea is a common problem caused by antibiotics which usually ends when the antibiotic is discontinued. Sometimes after starting treatment with antibiotics, patients can develop watery and bloody stools (with or without stomach cramps and fever) even as late as two or more months after having taken the last dose of the antibiotic. If this occurs, patients should contact their physician as soon as possible. Patients should be advised not to use antacid preparations containing magnesium trisilicate while taking Nitrofurantoin Oral Suspension, USP.

DRUG INTERACTIONS

Antacids containing magnesium trisilicate, when administered concomitantly with nitrofurantoin, reduce both the rate and extent of absorption. The mechanism for this interaction probably is adsorption of nitrofurantoin onto the surface of magnesium trisilicate.

Uricosuric drugs, such as probenecid and sulfinpyrazone, can inhibit renal tubular secretion of nitrofurantoin. The resulting increase in nitrofurantoin serum levels may increase toxicity, and the decreased urinary levels could lessen its efficacy as a urinary tract antibacterial.

DRUG/LABORATORY TEST INTERACTIONS

As a result of the presence of nitrofurantoin, a false-positive reaction for glucose in the urine may occur. This has been observed with Benedict’s and Fehling’s solutions but not the glucose enzymatic test.

Carcinogenesis, Mutagenesis, Impairment of Fertility

Nitrofurantoin was not carcinogenic when fed to female Holtzman rats for 44.5 weeks or to female Sprague-Dawley rats for 75 weeks.

Two chronic rodent bioassays utilizing male and female Sprague-Dawley rats and two chronic bioassays in Swiss mice and in BDF^1 mice revealed no evidence of carcinogenicity.

Nitrofurantoin presented evidence of carcinogenic activity in female B6C3F1 mice as shown by increased incidences of tubular adenomas, benign mixed tumors, and granulosa cell tumors of the ovary. In male F344/N rats, there were increased incidences of uncommon kidney tubular cell neoplasms, osteosarcomas of the bone, and neoplasms of the subcutaneous tissue. In one study involving subcutaneous administration of 75 mg/kg nitrofurantoin to pregnant female mice, lung papillary adenomas of unknown significance were observed in the F1 generation.

Nitrofurantoin has been shown to induce point mutations in certain strains of Salmonella typhimurium and forward mutations on L5178Y mouse lymphoma cells. Nitrofurantoin induced increased numbers of sister chromatid exchanges and chromosomal aberrations in Chinese hamster ovary cells but not in human cells in culture. Results of the sex-linked recessive lethal assay in Drosophila were negative after administration of nitrofurantoin by feeding or by injection. Nitrofurantoin did not induce heritable mutation in the rodent models examined.

The significance of carcinogenicity and mutagenicity findings relative to the therapeutic use of nitrofurantoin in humans is unknown.

The administration of high doses of nitrofurantoin to rats causes temporary spermatogenic arrest; this is reversible on discontinuing the drug. Doses of 10 mg/kg/day or greater in healthy human males may, in certain unpredictable instances, produce a slight to moderate spermatogenic arrest with a decrease in sperm count.

PREGNANCY:

Teratogenic effects:

Pregnancy Category B. Several reproduction studies have been performed in rabbits and rats at doses up to six times the human dose and have revealed no evidence of impaired fertility or harm to the fetus due to nitrofurantoin. In a single published study conducted in mice at 68 times the human dose (based on mg/kg administered to the dam), growth retardation and a low incidence of minor and common malformations were observed. However at 25 times the human dose, fetal malformations were not observed; the relevance of these findings to humans is uncertain. There are, however, no adequate and well-controlled studies in pregnant women. Because animal reproduction studies are not always predictive of human response, this drug should be used during pregnancy only if clearly needed.

Non-teratogenic effects:

Nitrofurantoin has been shown in one published transplacental carcinogenicity study to induce lung papillary adenomas in the F1 generation mice at doses 19 times the human dose on a mg/kg basis. The relationship of this finding to potential human carcinogenesis is presently unknown. Because of the uncertainty regarding the human implications of these animal data, this drug should be used during pregnancy only if clearly needed.

LABOR AND DELIVERY:

See CONTRAINDICATIONS.

Nursing Mothers

Nitrofurantoin has been detected in human breast milk in trace amounts. Because of the potential for serious adverse reactions from nitrofurantoin in nursing infants under one month of age, a decision should be made whether to discontinue nursing or to discontinue the drug, taking into account the importance of the drug to the mother. (See CONTRAINDICATIONS.)

Pediatric Use

Safety and effectiveness of Nitrofurantoin Oral Suspension, USP in neonates below the age of one month have not been established. (See CONTRAINDICATIONS.)

ADVERSE REACTIONS

Respiratory:

CHRONIC, SUBACUTE, OR ACUTE PULMONARY HYPERSENSITIVITY REACTIONS MAY OCCUR. CHRONIC PULMONARY REACTIONS MAY OCCUR GENERALLY IN PATIENTS WHO HAVE RECEIVED CONTINUOUS TREATMENT FOR SIX MONTHS OR LONGER. MALAISE, DYSPNEA ON EXERTION, COUGH, AND ALTERED PULMONARY FUNCTION ARE COMMON MANIFESTATIONS WHICH CAN OCCUR INSIDIOUSLY. RADIOLOGIC AND HISTOLOGIC FINDINGS OF DIFFUSE INTERSTITIAL PNEUMONITIS OR FIBROSIS, OR BOTH, ARE ALSO COMMON MANIFESTATIONS OF THE CHRONIC PULMONARY REACTION. FEVER IS RARELY PROMINENT.

THE SEVERITY OF CHRONIC PULMONARY REACTIONS AND THEIR DEGREES OF RESOLUTION APPEAR TO BE RELATED TO THE DURATION OF THERAPY AFTER THE FIRST CLINICAL SIGNS APPEAR. PULMONARY FUNCTION MAY BE IMPAIRED PERMANENTLY, EVEN AFTER CESSATION OF THERAPY. THE RISK IS GREATER WHEN CHRONIC PULMONARY REACTIONS ARE NOT RECOGNIZED EARLY.

In subacute pulmonary reactions, fever and eosinophilia occur less often than in the acute form. Upon cessation of therapy, recovery may require several months. If the symptoms are not recognized as being drug-related and nitrofurantoin therapy is not stopped, the symptoms may become more severe.

Acute pulmonary reactions are commonly manifested by fever, chills, cough, chest pain, dyspnea, pulmonary infiltration with consolidation of pleural effusion on x-ray, and eosinophilia. Acute reactions usually occur within the first week of treatment and are reversible with cessation of therapy. Resolution often is dramatic. (See WARNINGS.)

Changes in EKG (e.g., non-specific ST/T wave changes, bundle branch block) have been reported in association with pulmonary reactions.

Cyanosis has been reported rarely.

Hepatic:

Hepatic reactions, including hepatitis, cholestatic jaundice, chronic active hepatitis, and hepatic neurosis, occur rarely. (See WARNINGS.)

Neurologic:

Peripheral neuropathy, which may become severe or irreversible, has occurred. Fatalities have been reported Conditions such as renal impairment (creatinine clearance under 60 mL per minute or clinically significant elevated serum creatinine), anemia, diabetes mellitus, electrolyte imbalance, vitamin B deficiency, and debilitating diseases may increase the possibility of peripheral neuropathy. (See WARNINGS.)

Asthenia, vertigo, nystagmus, dizziness, headache, and drowsiness have also been reported with the use of nitrofurantoin.

Benign intracranial hypertension (pseudotumor cerebri), confusion, depression, optic neuritis, and psychotic reactions have been reported rarely. Bulging fontanels, as a sign of benign intracranial hypertension in infants, have been reported rarely.

Dermatologic:

Exfoliative dermatitis and erythema multiforme (including Stevens-Johnson syndrome) have been reported rarely. Transient alopecia also has been reported.

Allergic:

A lupus-like syndrome associated with pulmonary reactions to nitrofurantoin has been reported. Also, angioedema; maculopapular, erythematous, or eczematous eruptions; pruritus; urticaria; anaphylaxis; arthralgia; myalgia; drug fever; and vasculitis (sometimes associated with pulmonary reactions) have been reported. Hypersensitivity reactions present the most frequent spontaneously-reported adverse events in world-wide postmarketing experience with nitrofurantoin formulations.

Gastrointestinal:

Nausea, emesis, and anorexia occur most often. Abdominal pain and diarrhea are less common gastrointestinal reactions. These dose-related reactions can be minimized by reduction of dosage. Sialadenitis and pancreatitis have been reported. There have been sporadic reports of pseudomembranous colitis with the use of nitrofurantoin. The onset of pseudomembranous colitis symptoms may occur during or after antimicrobial treatment. (See WARNINGS.)

Hematologic:

Cyanosis secondary to methemoglobinemia has been reported rarely.

Miscellaneous:

As with other antimicrobial agents, superinfections caused by resistant organisms, e.g., Pseudomonas species or Candida species, can occur. There are sporadic reports of Clostridium difficile superinfections, or pseudomembranous colitis, with the use of nitrofurantoin.

Laboratory Adverse Events:

The following laboratory adverse events have been reported with the use of nitrofurantoin; increased AST (SGOT), increased ALT (SGPT), decreased hemoglobin, increased serum phosphorus, eosinophilia, glucose-6-phosphate dehydrogenase deficiency anemia (see WARNINGS), agranulocytosis, leukopenia, granulocytopenia, hemolytic anemia, thrombocytopenia, megaloblastic anemia. In most cases, these hematologic abnormalities resolved following cessation of therapy. Aplastic anemia has been reported rarely.

To report SUSPECTED ADVERSE REACTIONS, contact PAI Pharma at 1-800-845-8210 or FDA at 1-800-FDA-1088 or www.fda.gov/medwatch.

OVERDOSAGE

Occasional incidents of acute overdosage of Nitrofurantoin Oral Suspension, USP have not resulted in any specific symptoms other than vomiting. Induction of emesis is recommended. There is no specific antidote, but a high fluid intake should be maintained to promote urinary excretion of the drug. It is dialyzable.

DOSAGE AND ADMINISTRATION

Nitrofurantoin Oral Suspension, USP should be given with food to improve drug absorption and, in some patients, tolerance.

Adults:

50 to 100 mg four times a day — the lower dosage level is recommended for uncomplicated urinary tract infections.

Pediatric Patients:

5 to 7 mg/kg of body weight per 24 hours, given in four divided doses (contraindicated under one month of age).

The following table is based on an average weight in each range receiving 5 to 6 mg/kg of body weight per 24 hours, given in four divided doses. It can be used to calculate an average dose of Nitrofurantoin Oral Suspension, USP (25 mg/5 mL) for pediatric patients.

Table 3: Pediatric Dosing Table

Weight in Kilograms (kg) | Pediatric Doses (milliliters) and Frequency
7 kg to 11 kg | 2.5 mL Four times Daily
12 kg to 21 kg | 5 mL Four times Daily
22 kg to 30 kg 7.5 mL | Four times Daily
31 kg to 41 kg 10 mL | Four times Saily
42 kg or greater | See Adult Dose

Therapy should be continued for one week or for at least 3 days after sterility of the urine is obtained. Continued infection indicates the need for reevaluation.

For long-term suppressive therapy in adults, a reduction of dosage to 50 to 100 mg at bedtime may be adequate. For long-term suppressive therapy in pediatric patients, doses as low as 1 mg/kg per 24 hours, given in a single dose or in two divided doses, may be adequate. SEE WARNINGS SECTION REGARDING RISKS ASSOCIATED WITH LONG TERM THERAPY.

HOW SUPPLIED

Nitrofurantoin Oral Suspension, USP is a lemon yellow liquid with a fruity scent available in:

NDC 0121-1996-10: 10 mL unit dose cup. Case contains 10 unit-dose cups of 10 mL (NDC 0121-1996-95), packaged in one tray of 10 unit-dose cups each.

Avoid exposure to strong light which may darken the drug. This package is child-resistant. Store at 20˚ to 25˚C (68˚ to 77˚F); excursions permitted to 15˚ to 30˚C (59˚ to 86˚F) [See USP for Controlled Room Temperature]. Protect from freezing. Shake vigorously. Use within 90 days

Keep this and all medication out of the reach of children.

Distributed by:

PAI Pharma
Greenville, SC 29605

R01/24

PRINCIPAL DISPLAY PANEL

NDC 0121-1996-05

Nitrofurantoin Oral Suspension, USP
50 mg/10 mL
FOR ORAL USE ONLY

A0998100124